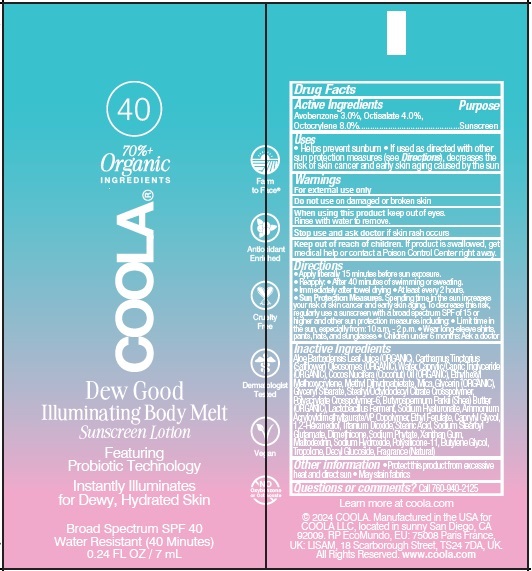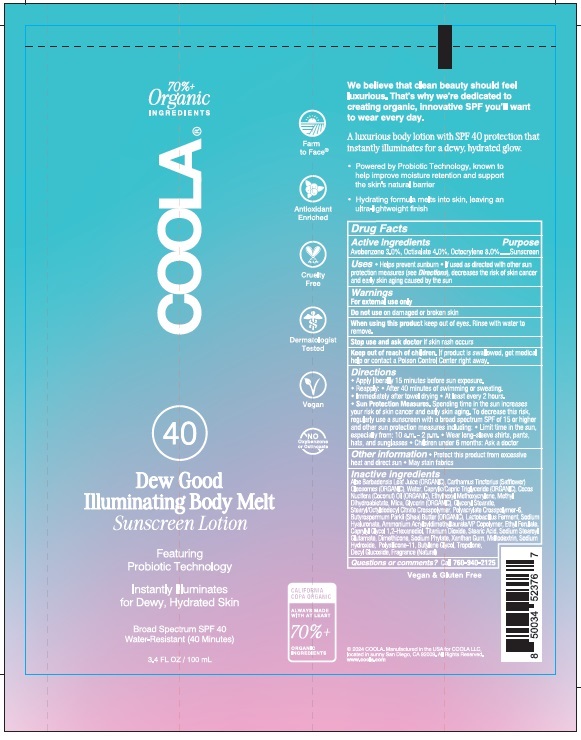 DRUG LABEL: COOLA Dew Good Illuminating Body Melt SPF 40
NDC: 79753-082 | Form: CREAM
Manufacturer: COOLA LLC
Category: otc | Type: HUMAN OTC DRUG LABEL
Date: 20240916

ACTIVE INGREDIENTS: AVOBENZONE 3.0 g/100 mL; OCTISALATE 4.0 g/100 mL; OCTOCRYLENE 8.0 g/100 mL
INACTIVE INGREDIENTS: ALOE VERA LEAF; SAFFLOWER; WATER; MEDIUM-CHAIN TRIGLYCERIDES; COCONUT OIL; ETHYLHEXYL METHOXYCRYLENE; METHYL DIHYDROABIETATE; MICA; GLYCERIN; GLYCERYL MONOSTEARATE; STEARYL/OCTYLDODECYL CITRATE CROSSPOLYMER; AMMONIUM ACRYLOYLDIMETHYLTAURATE, DIMETHYLACRYLAMIDE, LAURYL METHACRYLATE AND LAURETH-4 METHACRYLATE COPOLYMER, TRIMETHYLOLPROPANE TRIACRYLATE CROSSLINKED (45000 MPA.S); SHEA BUTTER; LIMOSILACTOBACILLUS FERMENTUM; HYALURONATE SODIUM; AMMONIUM ACRYLOYLDIMETHYLTAURATE/VP COPOLYMER; ETHYL FERULATE; CAPRYLYL GLYCOL; 1,2-HEXANEDIOL; TITANIUM DIOXIDE; STEARIC ACID; SODIUM STEAROYL GLUTAMATE; PHYTATE SODIUM; DIMETHICONE; XANTHAN GUM; MALTODEXTRIN; SODIUM HYDROXIDE; DIMETHICONE/VINYL DIMETHICONE CROSSPOLYMER (SOFT PARTICLE); BUTYLENE GLYCOL; TROPOLONE; DECYL GLUCOSIDE

Dew Good Illuminating Body Melt Sunscreen Lotion

ACTIVE INGREDIENT

Avobenzone – 3.0%
Octisalate – 4.0%
Octocrylene – 8.0%

Purpose

Sunscreen

Uses

• Helps prevent sunburn • If used as directed with other sun

protection measures (see Directions), decreases the risk of skin cancer

and early skin aging caused by the sun.

Warnings

For external use only.
Do not use on damaged or broken skin.
When using this product keep out of eyes. Rinse with water to remove.
Stop use and ask doctor if skin rash occurs

Keep out of reach of children. If product is swallowed, get medical

help or contact a Poison Control Center right away.

Directions

• Apply liberally 15 minutes before sun exposure
• Reapply: • After 40 minutes of swimming or sweating.
• Immediately after towel drying. • Apply at least every 2 hours.
• Sun Protection Measures. Spending time in the sun increases
your risk of skin cancer and early skin aging. To decrease this risk
regularly use a sunscreen with a broad spectrum SPF value of 15 or higher
and other sun protection measures including: • Limit time in the sun,
especially from 10 a.m. to 2 p.m. • Wear long-sleeved shirts, pants,
hats, and sunglasses. • Children under 6 months: Ask a doctor.

Other information • Protect this product from excesssive

heat and direct sun • May stain fabrics

Inactive ingredients
Aloe Barbadensis Leaf Juice (ORGANIC), Carthamus Tinctorius (Safflower),
Oleosomes (ORGANIC), Water, Caprylic/Capric Triglyceride (ORGANIC), Cocos
Nucifera (Coconut) Oil (ORGANIC), Ethylhexyl Methoxycrylene, Methyl
Dihydroabietate, Mica, Glycerin (ORGANIC), Glyceryl Stearate,
Stearyl/Octyldodecyl Citrate Crosspolymer, Polyacrylate Crosspolymer-6,
Butyrospermum Parkii (Shea) Butter (ORGANIC), Lactobacillus Ferment, Sodium
Hyaluronate, Ammonium Acryloyldimethyltaurate/VP Copolymer, Ethyl Ferulate,
Caprylyl Glycol, 1,2-Hexanediol, Titanium Dioxide, Stearic Acid, Sodium Stearoyl
Glutamate, Dimethicone, Sodium Phytate, Xanthan Gum, Maltodextrin, Sodium
Hydroxide, Polysilicone-11, Butylene Glycol, Tropolone,
Decyl Glucoside, Fragrance (Natural)

Questions or Comments? Call 760-940-2125

PACKAGE LABEL

Dew Good

Illuminating Body Melt

Sunscreen Lotion

Broad Spectrum SPF 40

3.4 FL. OZ. / 100 mL

2024 COOLA. Manufactured in the USA for COOLA LLC,

located in sunny San Diego, CA 92009

www.coola.com

100 mL Bottle

7 mL Tube

res